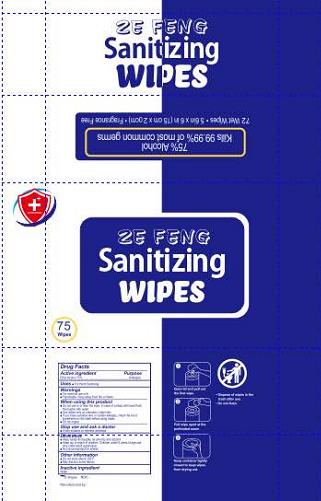 DRUG LABEL: wet wipes
NDC: 80332-002 | Form: CLOTH
Manufacturer: Quzhou Zefeng Import& Export Co., Ltd.
Category: otc | Type: HUMAN OTC DRUG LABEL
Date: 20200902

ACTIVE INGREDIENTS: ALCOHOL 0.75 g/1 g
INACTIVE INGREDIENTS: WATER

zefeng 75

Active Ingredient(s)

Alcohol 75% v/v. Purpose: Antiseptic

Purpose

Antiseptic, wet wipes

Use

Wet wipes to help reduce bacteria that potentially can cause disease. For use when soap and water are not available.

Warnings

For external use only. Flammable. Keep away from heat or flame

Do not use

- in children less than 2 months of age
- on open skin wounds

When using this product keep out of eyes, ears, and mouth. In case of contact with eyes, rinse eyes thoroughly with water.
Stop use and ask a doctor if irritation or rash occurs. These may be signs of a serious condition.
Keep out of reach of children. If swallowed, get medical help or contact a Poison Control Center right away.

Stop use and ask a doctor if irritation or rash occurs. These may be signs of a serious condition.

Keep out of reach of children. If swallowed, get medical help or contact a Poison Control Center right away.

Directions

- Supervise children under 6 years of age when using this product to avoid swallowing.

Other information

- Store between 15-30C (59-86F)
- Avoid freezing and excessive heat above 40C (104F)

Inactive ingredients

WATER

Package Label - Principal Display Panel

75PCS NDC: 80332-002-01